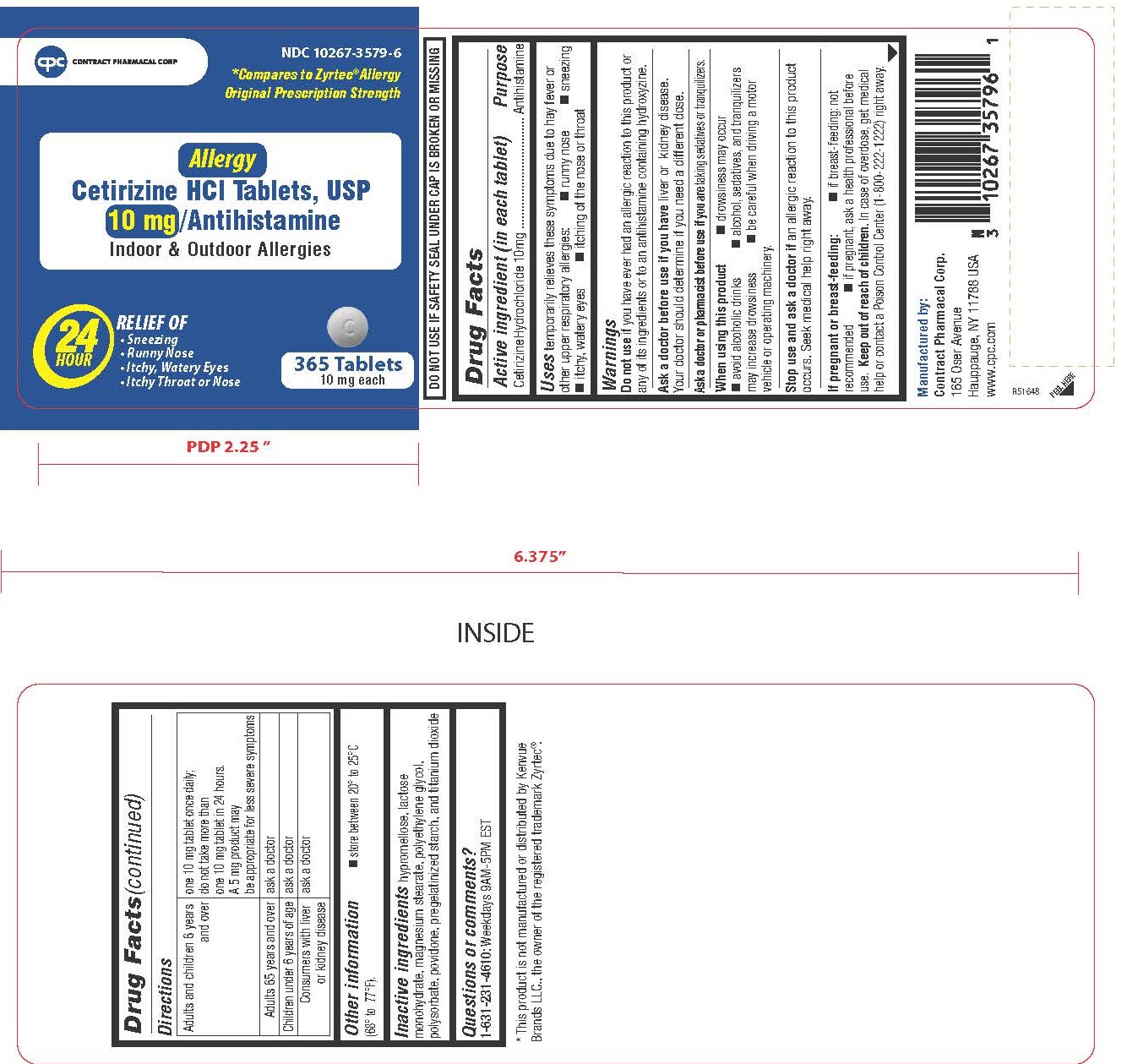 DRUG LABEL: Cetirizine Hydrochloride 10 mg
NDC: 10267-3579 | Form: TABLET, FILM COATED
Manufacturer: Contract Pharmacal Corp.
Category: otc | Type: HUMAN OTC DRUG LABEL
Date: 20250528

ACTIVE INGREDIENTS: CETIRIZINE HYDROCHLORIDE 10 mg/1 1
INACTIVE INGREDIENTS: LACTOSE MONOHYDRATE; STARCH, CORN; POVIDONE K30; MAGNESIUM STEARATE; TITANIUM DIOXIDE; HYPROMELLOSES; POLYETHYLENE GLYCOL 400; POLYSORBATE 80

3579

Drug Facts

Active ingredient (in each tablet)

Cetirizine Hydrochloride 10 mg

Purpose

Antihistamine

Uses

temporarily relieves these symptoms due to hay fever or other upper respiratory allergies:

 runny nose

 sneezing

 itchy, watery eyes

 itching of the nose or throat

WARNINGS

Do not use if you have ever had an allergic reaction to this product or any of its ingredients or to an antihistamine containing hydroxyzine.

Ask a doctor before use if you have liver or kidney disease. Your doctor should determine if you need a different dose.

Ask a doctor or pharmacist before use if you are taking sedatives or tranquilizers.

When using this product

 drowsiness may occur

 avoid alcoholic drinks

alcohol, sedatives, and tranquilizers may increase drowsiness

 be careful when driving a motor vehicle or operating machinery.

Stop use and ask a doctor if an allergic reaction to this product occurs. Seek medical help right away.

If pregnant or breast-feeding:

 if breast-feeding: not recommended

 if pregnant: ask a health professional before use.

Keep out of reach of children. In case of overdose, get medical help or contact a Poison Control Center (1-800-222-1222) right away.

Directions

Adults and children 6 years and over | one 10 mg tablet once daily; do not take more than one 10 mg tablet in 24 hours. A 5 mg product may be appropriate for less severe symptoms.
Adults 65 years and over | ask a doctor
Children under 6 years of age | ask a doctor
Consumers with liver or kidney disease | ask a doctor

Other information

store between 20° to 25°C (68° to 77°F).

INACTIVE INGREDIENT

hypromellose, lactose monohydrate, magnesium stearate, polyethylene glycol, polysorbate, povidone, pregelatinized starch, and titanium dioxide.

QUESTIONS

1-800-231-4670

DO NOT USE IF SAFETY SEAL UNDER CAP IS BROKEN OR MISSING

Manufactured by:
Contract Pharmacal Corp.
165 Oser Avenue
Hauppauge, NY 11788 USA
www.cpc.com

* This product is not manufactured or distributed by Kenvue Brands LLC., the owner of the registered trademark Zyrtec®.

PACKAGE LABEL

NDC 10267-3579-6
*Compares to Zyrtec®Allergy Original Prescription Strength

Allergy

Cetirizine HCl Tablets, USP

10mg/ Antihistamine

Indoor & Outdoor Allergies

24 Hour

RELIEF OF
• Sneezing
• Runny Nose
• Itchy, Watery Eyes
• Itchy Throat or Nose

365 Tablets

10 mg each